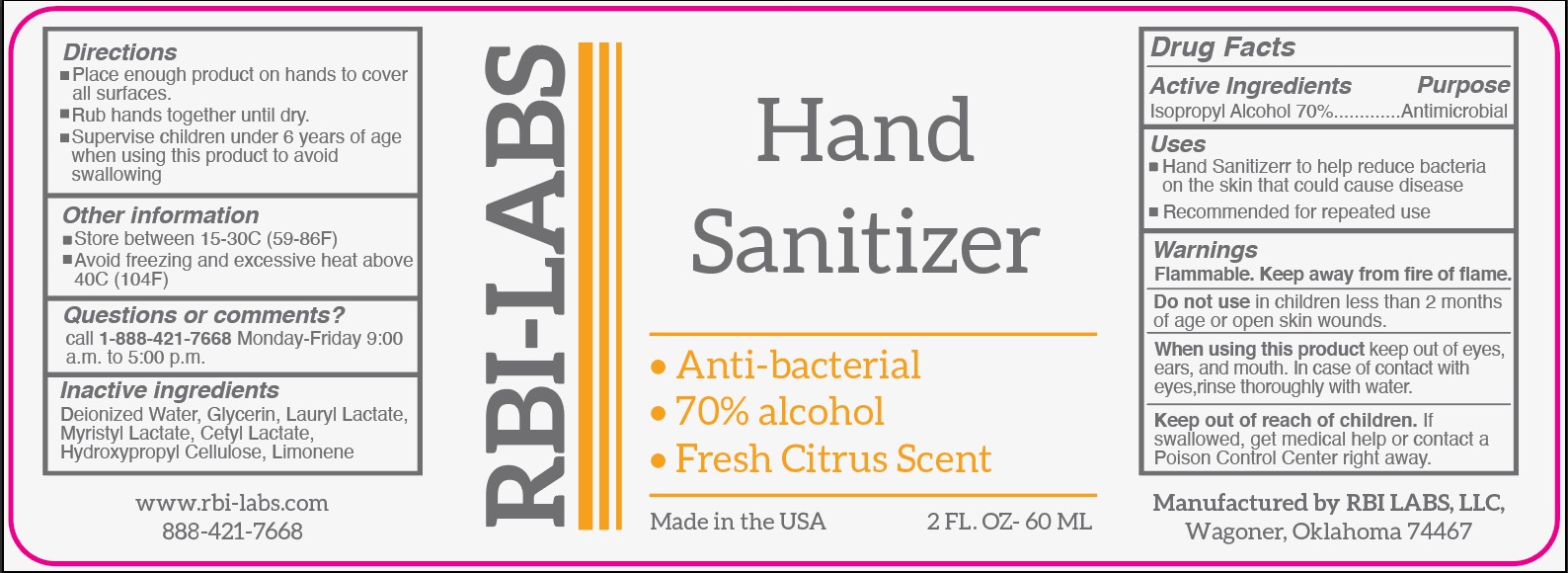 DRUG LABEL: Hand Sanitizer
NDC: 80932-001 | Form: SOLUTION
Manufacturer: ROOTS BEAUTY INNOVATIONS LLC
Category: otc | Type: HUMAN OTC DRUG LABEL
Date: 20220201

ACTIVE INGREDIENTS: ISOPROPYL ALCOHOL 70 mL/100 mL
INACTIVE INGREDIENTS: MYRISTYL LACTATE; CETYL LACTATE; LOW-SUBSTITUTED HYDROXYPROPYL CELLULOSE, UNSPECIFIED; LIMONENE, (+)-; GLYCERIN; LAURYL LACTATE; WATER

Active Ingredient(s)

Isopropyl Alcohol 70%

Purpose

Antimicrobial

Use

Hand Sanitizer to help reduce bacteria that potentially can cause disease. For use when soap and water are not available.

Directions

- Place enough product on hands to cover all surfaces.
- Rub hands together until dry.
- Supervise children under 6 years of age when using this product to avoid swallowing.

Warnings

For external use only

Flammable. Keep away from heat or flame.

Do not use

- in children less than 2 months of age
- on open skin wounds

When using this product keep out of eyes, ears, and mouth. Do not ingest. In case of contact with eyes, rinse eyes thoroughly with water.

Stop use and ask a doctor if irritation or rash occurs. These may be signs of a serious condition.

Keep out of reach of children. If swallowed, get medical help or contact a Poison Control Center right away.

Other information

- Store between 15-30C (59-86F)
- Avoid freezing and excessive heat above 40C (104F)

Inactive ingredients

Deionized Water, Glycerin, Lauryl Lactate, Myristyl Lactate, Cetyl Lactate, Hydroxypropyl Cellulose, Limonene

Package Label - Principal Display Panel

60 ml NDC: 80932-001-06